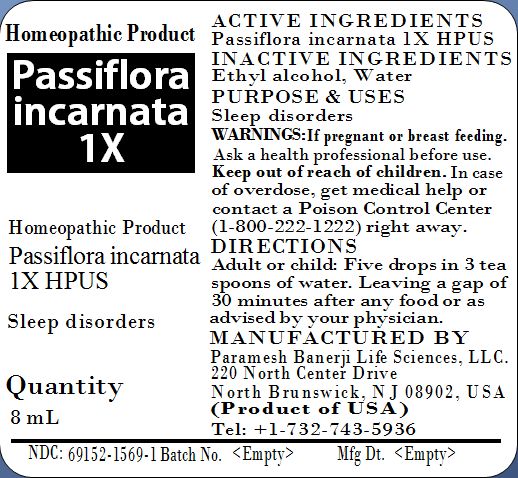 DRUG LABEL: Passiflora incarnata 1X
NDC: 69152-1569 | Form: LIQUID
Manufacturer: Paramesh Banerji Life Sciences LLC
Category: homeopathic | Type: HUMAN OTC DRUG LABEL
Date: 20150529

ACTIVE INGREDIENTS: PASSIFLORA INCARNATA FLOWERING TOP 1 [hp_X]/8 mL
INACTIVE INGREDIENTS: ALCOHOL; WATER

Active Ingredients

Passiflora incarnata 1X HPUS

Inactive Ingredients

Ethyl alcohol, Water

Purpose

Sleep disorders

Uses

Sleep disorders

Warnings

If pregnant or breast feeding ask a health professional before use.

Keep out of reach of children. In case of overdose, get medical help or contact a Poison Control Center (1-800-222-1222) right away.

Direction

Adult or child: Five drops in 3 tea spoons of water, leaving a gap of 30 minutes from any food or as advised by your physician.

Manufactured by

Paramesh Banerji Life Sciences, LLC

220 North Center Drive

North Brunswick, NJ 08902, USA

Product of USA

Tel: +1-732-743-5936

Principal Display Panel

Homeopathic Product

Passiflora incarnata 1X

Homeopathic Product

Passiflora incarnata 1X HPUS

Sleep disorders

Quantity

8mL